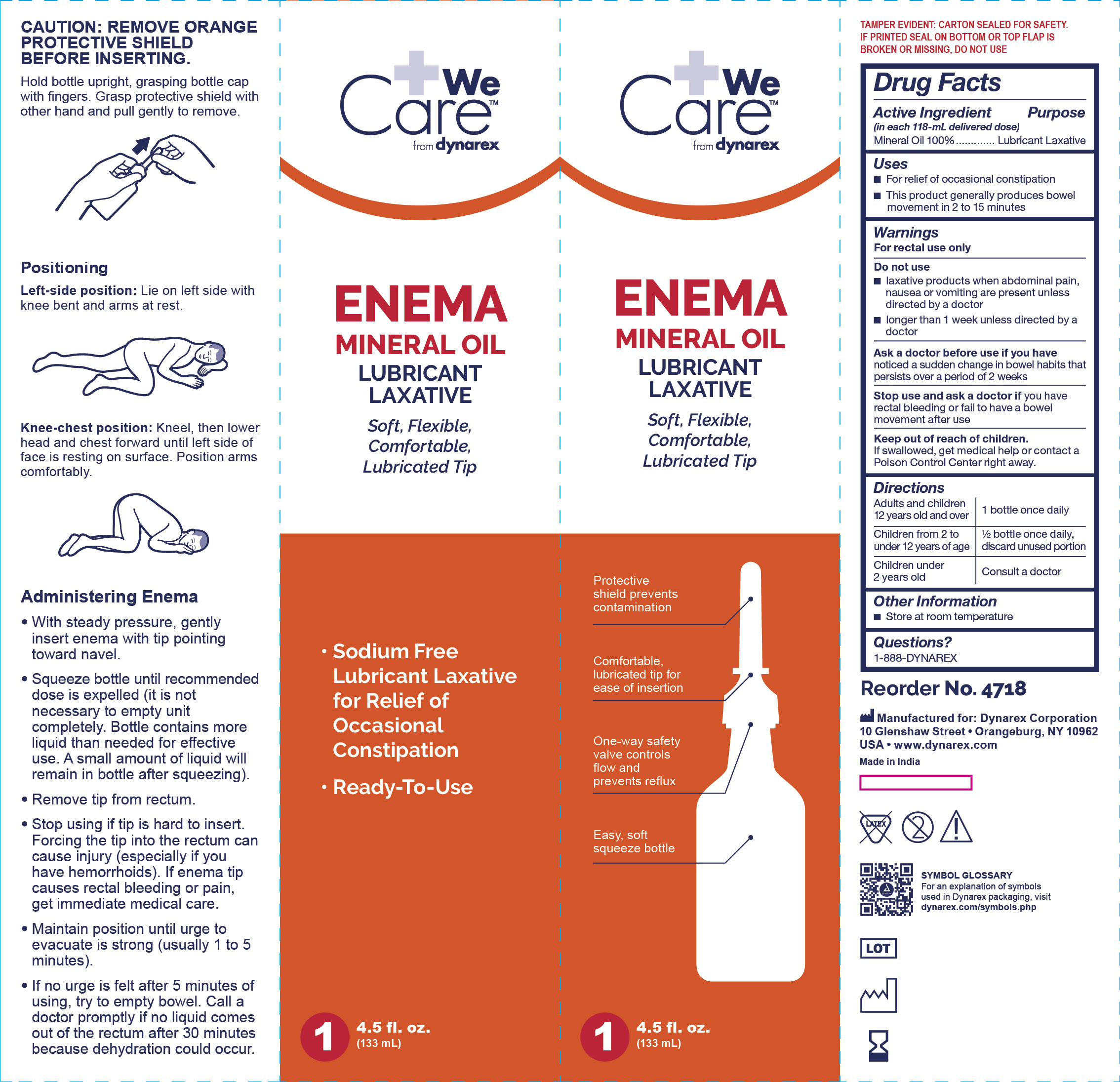 DRUG LABEL: 4718 Enema, Mineral Oil
NDC: 67777-430 | Form: ENEMA
Manufacturer: Dynarex
Category: otc | Type: HUMAN OTC DRUG LABEL
Date: 20241120

ACTIVE INGREDIENTS: MINERAL OIL 133 g/133 mL

4718 Enema, Mineral Oil 67777-430-01

Active Ingredient

Mineral Oil 100%

Purpose

Lubricant Laxative

Uses

- For relief of occasional constipation.
- This product generally produces bowel movement in 2 to 15 minutes.

Warnings

For rectal use only.

Do not use

- Laxative products when abdominal pain, nausea or vomiting are present unless directed by a doctor.
- Longer than one week unless directed by a doctor.

Ask a doctor before use if you have

- Noticed a sudden change in bowel habits that persists over a period of two weeks.

Stop use and ask a doctor if

- You have rectal bleeding or fail to have a bowel movement after use.

Keep out of reach of children.

- If swallowed, get medical help or contact a Poison Control Center right away.

Directions

- Adults and children 12 years old and older: 1 bottle daily.
- Children from 2 to under 12 years of age: 1/2 bottle once daily.
- Children under 2 years old: Consult a doctor.

Other information

- Store at room temperature.

Questions?

- 1-888-Dynarex

Label

Enema, Mineral Oil, 4718